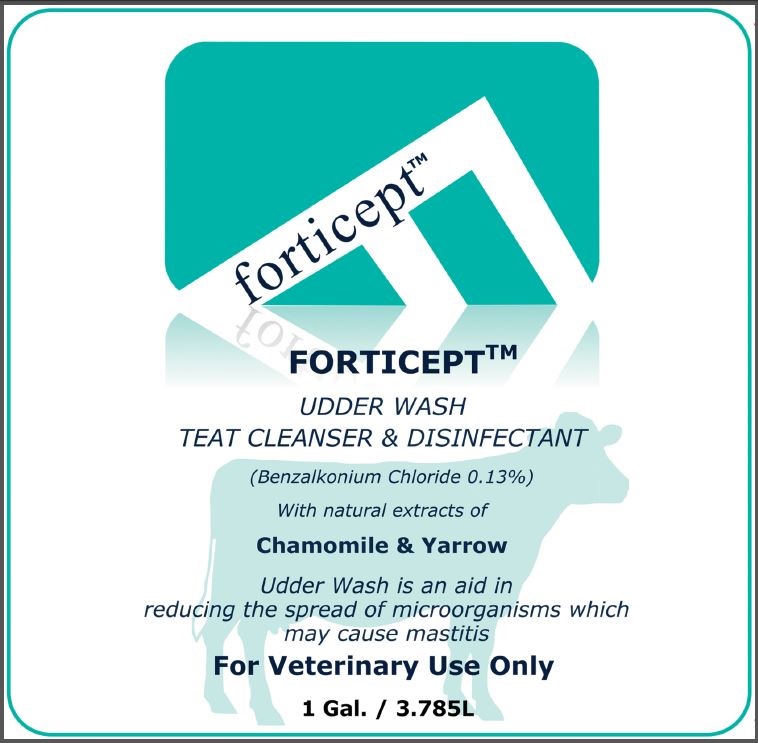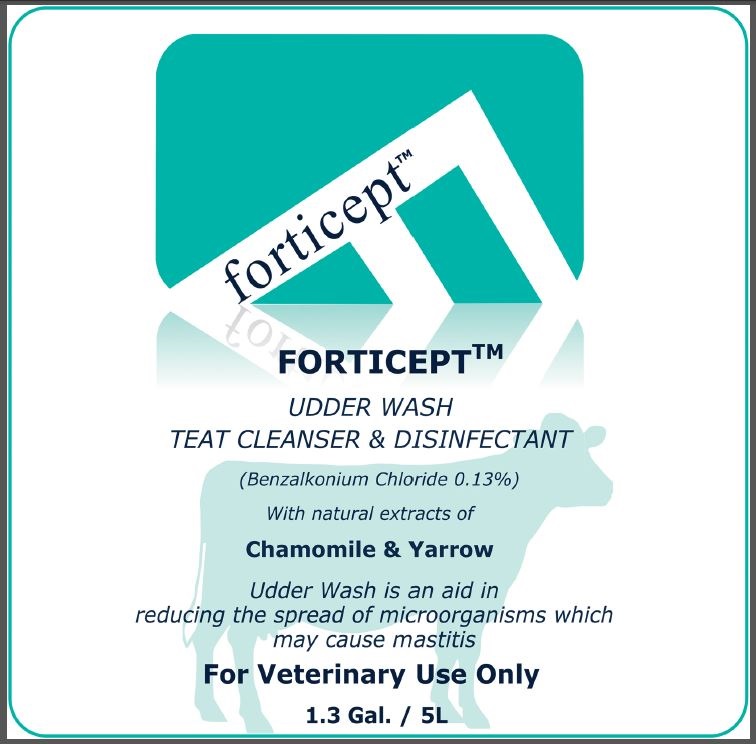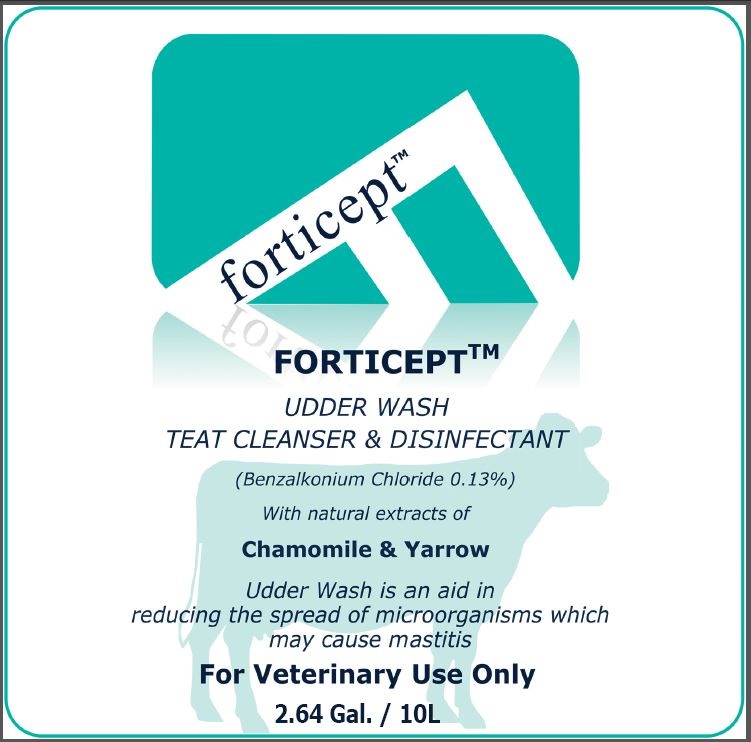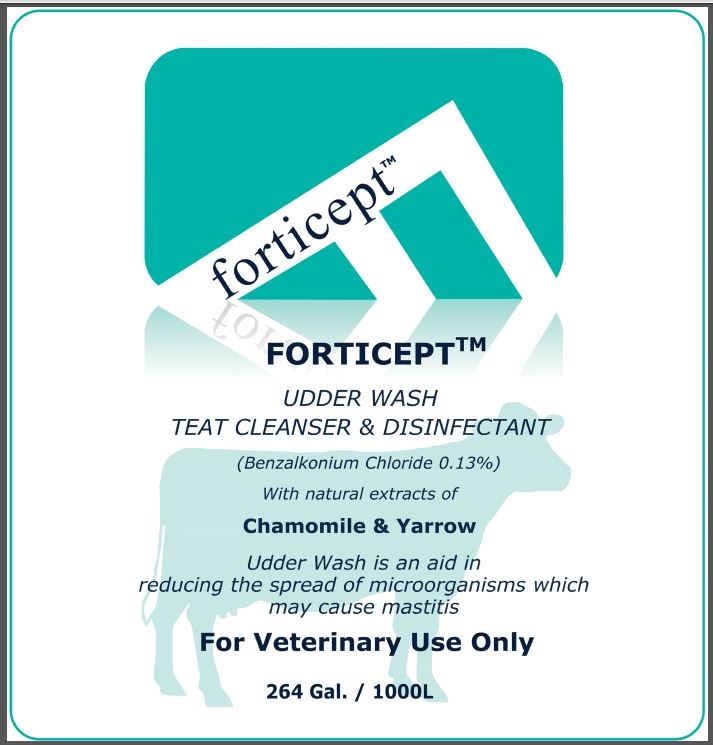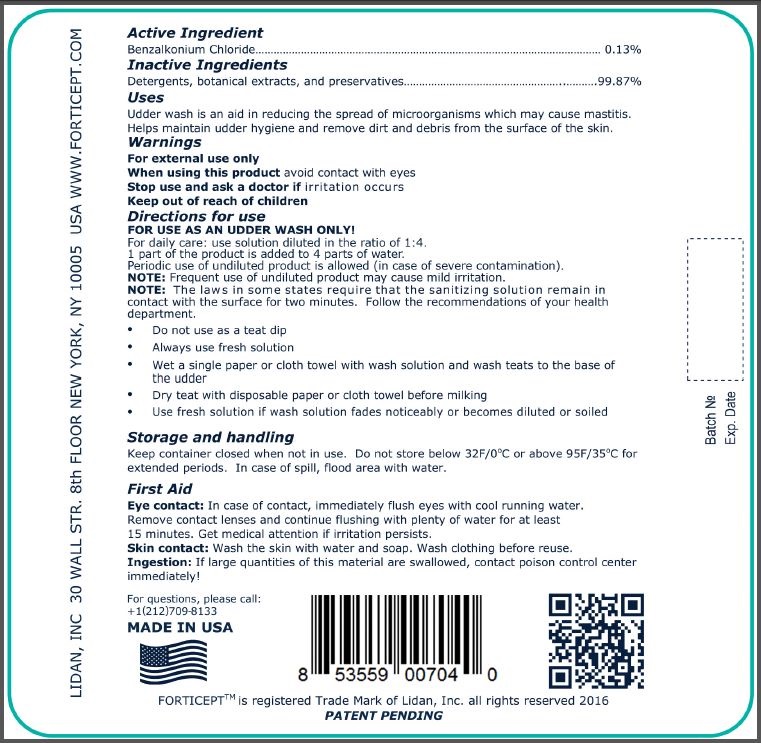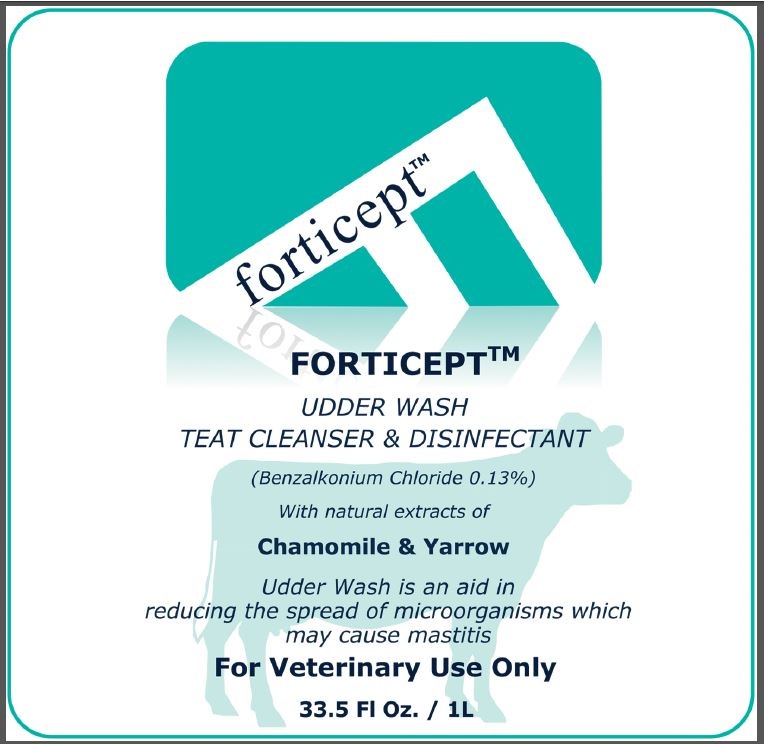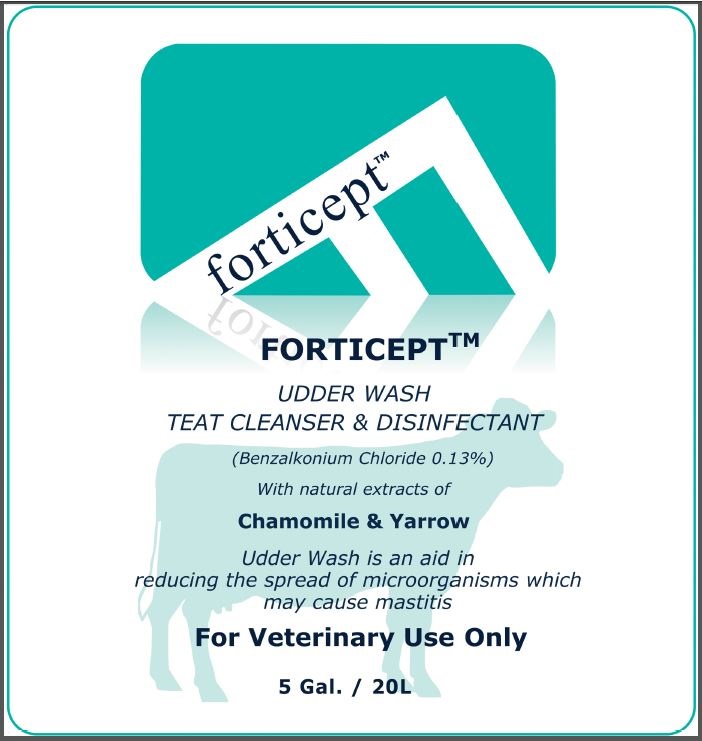 DRUG LABEL: Forticept Udder Wash Teat Cleanser and Disinfectant
NDC: 72127-0501 | Form: LIQUID
Manufacturer: LIDAN, INC.
Category: animal | Type: OTC ANIMAL DRUG LABEL
Date: 20240927

ACTIVE INGREDIENTS: BENZALKONIUM CHLORIDE 13 g/1 L

Forticept Udder Wash Teat Cleanser and Disinfectant

Active Ingredients

Benzalkonium Chloride 0.13%

Inactive Ingredients

Detergents, botanical extracts, and preservatives...99.87%

Uses

Udder wash is an aid in reducing the spread of microorganisms which may cause mastitis. Helps maintain udder hygiene and remove dirt and debris from the surface of the skin.

Warnings

For external use only

When using this product

avoid contact with eyes

Stop use and ask a doctor if

irritation occurs

Directions for use

FOR USE AS AN UDDER WASH ONLY!

For daily care: use solution diluted in the ratio of 1:4

1 part of the product is added to 4 parts of water.

Periodic use of undiluted product is allowed (in case of severe contamination).

NOTE: Frequent use of undiluted product may cause mild irritation.

NOTE: The laws in some states require that the sanitizing solution remain in contact with the surface for two minutes. Follow the recommendations of your health department.

- Do not use as a teat dip
- Always use fresh solution
- Wet a single paper or cloth towel with wash solution and wash teats to the base of the udder
- Dry teat with disposable paper or cloth towel before milking
- Use fresh solution if wash solution fades noticeably or becomes diluted or soiled

Storage and handling

Keep container closed when not in use. Do not store below 32F/0°C or above 95F/35°C for extended periods. In case of spill, flood area with water.

FIRST AID

Eye contact: In case of contact, immediately flush eyes with cool running water.

Remove contact lenses and continue flushing with plenty of water for at least 15 minutes. Get medical attention if irritation persists.

Skin contact: Wash the skin with water and soap. Wash clothing before reuse.

Ingestion: If large quantities of this material are swallowed, call a poison control center immediately.

Questions

For questions, please call:

+1(212)709-8133